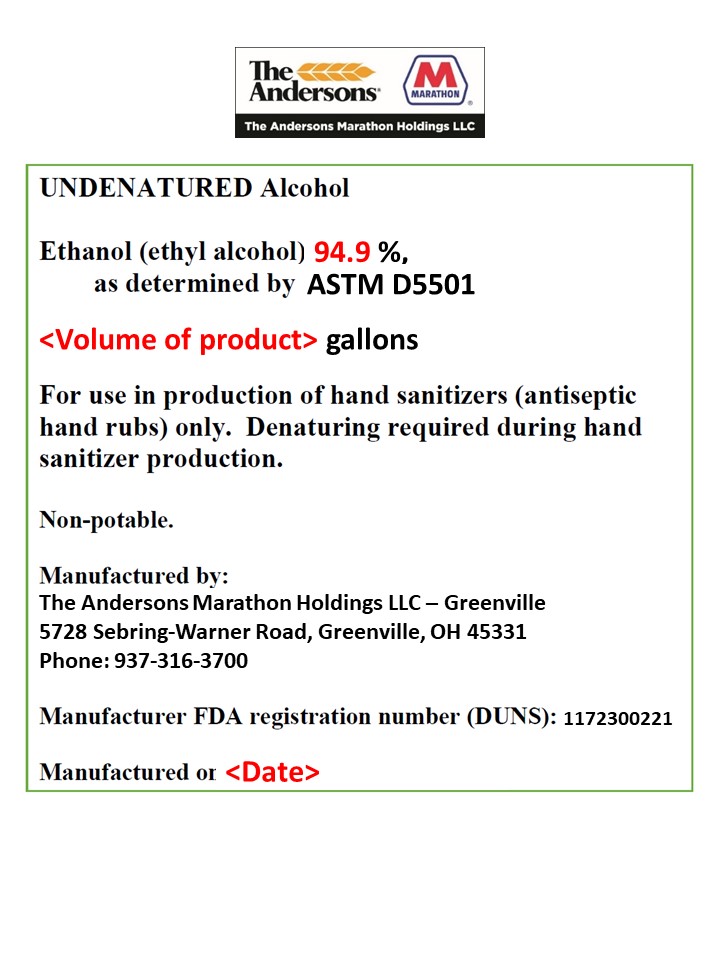 DRUG LABEL: Undenatured Alcohol
NDC: 75128-190 | Form: LIQUID
Manufacturer: The Andersons Marathon Holdings LLC
Category: otc | Type: HUMAN OTC DRUG LABEL
Date: 20200409

ACTIVE INGREDIENTS: ALCOHOL 19000 kg/20000 kg
INACTIVE INGREDIENTS: WATER 1000 kg/20000 kg

Ingredient for hand sanitizer

Active Ingredient(s)

Alcohol 80% v/v. Purpose: Antiseptic

Purpose

Antiseptic, Hand Sanitizer

INACTIVE INGREDIENT

Contains water

Use

For use in production of hand sanitizers (antiseptic hand rubs) only. Denaturing required during hand sanitizer production.

Warnings

Non-potable. Flammable. Keep away from heat or flame

DOSAGE AND ADMINISTRATION

For use in production of hand sanitizers only.

Non-potable. Keep out of reach of children

Package Label - Principal Display Panel

NDC: 00000-000-00